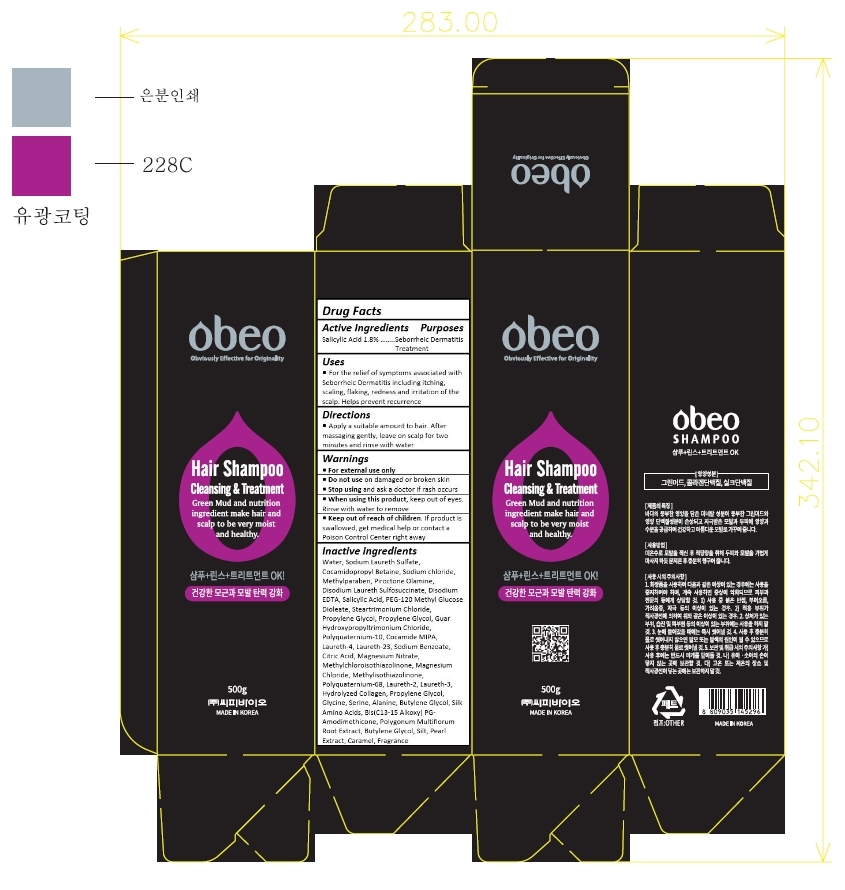 DRUG LABEL: Obeo Hair
NDC: 69871-007 | Form: SHAMPOO
Manufacturer: CPbio Co., Ltd
Category: otc | Type: HUMAN OTC DRUG LABEL
Date: 20170515

ACTIVE INGREDIENTS: SALICYLIC ACID 9 mg/500 g
INACTIVE INGREDIENTS: WATER; SODIUM LAURETH-3 SULFATE; COCAMIDOPROPYL BETAINE; SODIUM CHLORIDE; METHYLPARABEN; PIROCTONE OLAMINE; DISODIUM LAURETH SULFOSUCCINATE; EDETATE DISODIUM; PEG-120 METHYL GLUCOSE DIOLEATE; TRIMETHYL OCTADECYL AMMONIUM CHLORIDE; PROPYLENE GLYCOL; GUAR HYDROXYPROPYLTRIMONIUM CHLORIDE (1.7 SUBSTITUENTS PER SACCHARIDE); POLYQUATERNIUM-10 (1000 MPA.S AT 2%); COCO MONOISOPROPANOLAMIDE; DIMETHICONE; LAURETH-4; LAURETH-23; SODIUM BENZOATE; CITRIC ACID MONOHYDRATE; MAGNESIUM NITRATE; METHYLCHLOROISOTHIAZOLINONE; MAGNESIUM CHLORIDE; METHYLISOTHIAZOLINONE; POLYQUATERNIUM-68; LAURETH-2; LAURETH-3; GLYCINE; SERINE; ALANINE; BUTYLENE GLYCOL; AMINO ACIDS, SILK; FALLOPIA MULTIFLORA ROOT; PEARL (HYRIOPSIS CUMINGII); CARAMEL

Drug Facts

ACTIVE INGREDIENT

Salicylic Acid 1.8%

PURPOSE

Seborrheic Dermatitis Treatment

INDICATIONS AND USAGE

For the relief of symptoms associated with Seborrheic Dermatitis including itching, scaling, flaking, redness and
irritation of the scalp. Helps prevent recurrence

DOSAGE AND ADMINISTRATION

Apply a suitable amount to hair. After massaging gently, leave on scalp for two minutes and rinse with water

WARNINGS

For external use only

Do not use on damaged or broken skin

Stop using and ask a doctor if rash occurs

When using this product, keep out of eyes. Rinse with water to remove

Keep out of reach of children. If product is swallowed, get medical help or contact a Poison Control Center right away.

INACTIVE INGREDIENT

Water, Sodium Laureth Sulfate, Cocamidopropyl Betaine, Sodium chloride, Methylparaben, Piroctone Olamine, Disodium Laureth Sulfosuccinate, Disodium EDTA, Salicylic Acid, PEG-120 Methyl Glucose Dioleate, Steartrimonium Chloride, Propylene Glycol, Propylene Glycol, Guar Hydroxypropyltrimonium Chloride, Polyquaternium-10, Cocamide MIPA, Laureth-4, Laureth-23, Sodium Benzoate, Citric Acid, Magnesium Nitrate, Methylchloroisothiazolinone, Magnesium Chloride, Methylisothiazolinone, Polyquaternium-68, Laureth-2, Laureth-3, Hydrolyzed Collagen, Propylene Glycol, Glycine, Serine, Alanine, Butylene Glycol, Silk Amino Acids, Bis(C13-15 Alkoxy) PG-Amodimethicone, Polygonum Multiflorum Root Extract, Butylene Glycol, Silt, Pearl Extract, Caramel, Fragrance